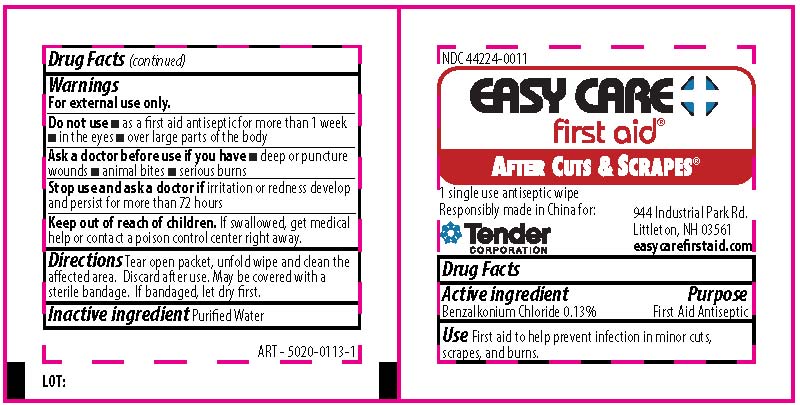 DRUG LABEL: Easy Care First Aid After Cuts and Scrapes Wipe
NDC: 44224-0011 | Form: SWAB
Manufacturer: Tender Corporation
Category: otc | Type: HUMAN OTC DRUG LABEL
Date: 20190926

ACTIVE INGREDIENTS: BENZALKONIUM CHLORIDE 1.3 mg/1 mL
INACTIVE INGREDIENTS: WATER

Easy Care First Aid After Cuts and Scrapes Wipe

Active Ingredient

Benzalkonium Chloride 0.13%

Purpose

First Aid Antiseptic

Use

First aid to help prevent infection in minor cuts, scrapes, and burns.

Warnings

For external use only

Do not use

- as a first aid antiseptic for more than 1 week
- in the eyes
- over large parts of the body

Stop use and ask a doctor if

Irritation or redness develop and persist for more than 72 hours.

Keep out of reach of children

If swallowed, get medical help or contact a Poison Control Center right away.

Directions

Tear open packet, unfold towelette and use to cleanse affected area. Discard after use. May be covered with a sterile bandage. If bandaged, let dry first.

Inactive Ingredient

Purified water

PACKAGE LABEL

Easy Care First Aid

After Cuts & Scrapes

1 single use antiseptic wipe

Responsibly made in China for:

Tender Corporation
944 Industrial Park Rd.

Littleton, NH 03561

easycarefirstaid.com